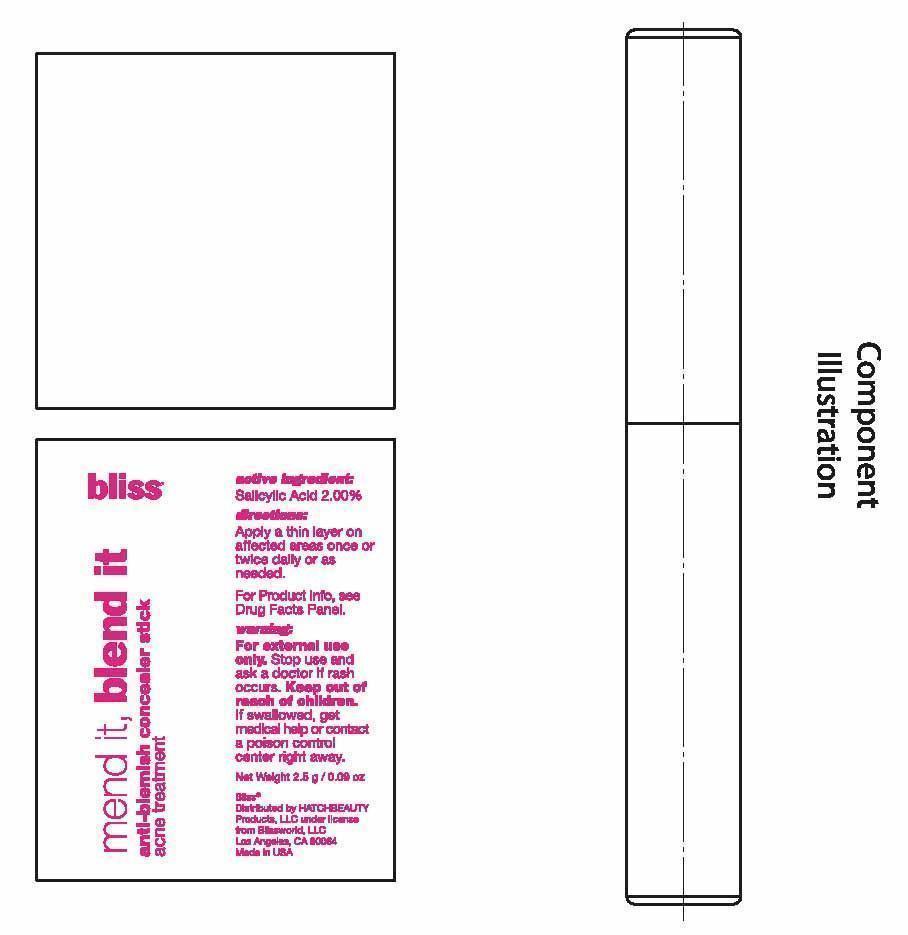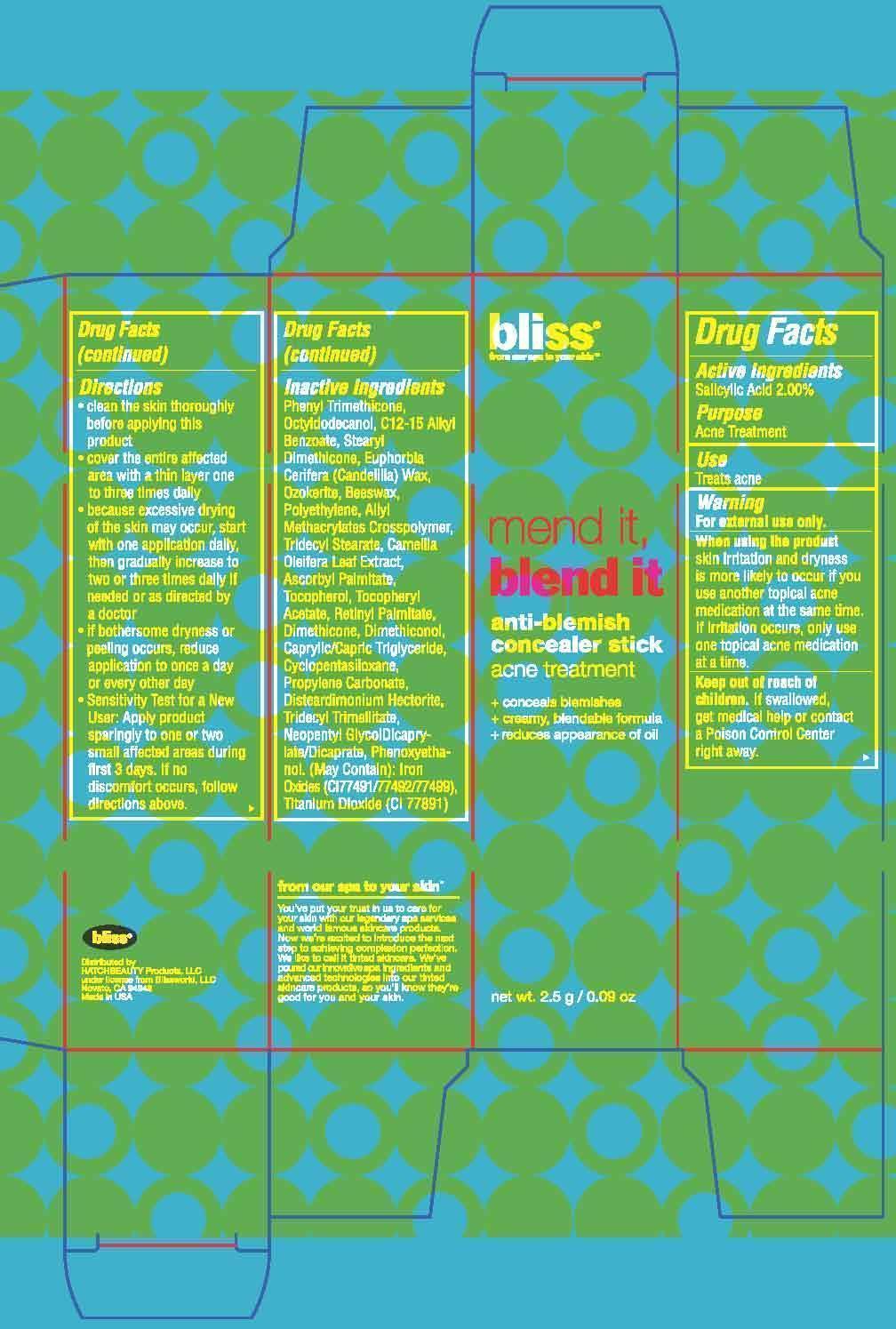 DRUG LABEL: ANTI-BLEMISH CONCEALER
NDC: 69863-201 | Form: STICK
Manufacturer: HATCHBEAUTY PRODUCTS LLC
Category: otc | Type: HUMAN OTC DRUG LABEL
Date: 20150623

ACTIVE INGREDIENTS: SALICYLIC ACID 2 g/100 g
INACTIVE INGREDIENTS: PHENYL TRIMETHICONE; OCTYLDODECANOL; C12-15 ALKYL BENZOATE; STEARYL DIMETHICONE (400 MPA.S AT 50C); CANDELILLA WAX; CERESIN; YELLOW WAX; HIGH DENSITY POLYETHYLENE; ALLYL METHACRYLATE/GLYCOL DIMETHACRYLATE CROSSPOLYMER; TRIDECYL STEARATE; CAMELLIA OLEIFERA LEAF; ASCORBYL PALMITATE; TOCOPHEROL; .ALPHA.-TOCOPHEROL ACETATE; VITAMIN A PALMITATE; DIMETHICONE; DIMETHICONOL (2000 CST); MEDIUM-CHAIN TRIGLYCERIDES; CYCLOMETHICONE 5; PROPYLENE CARBONATE; DISTEARDIMONIUM HECTORITE; TRIDECYL TRIMELLITATE; NEOPENTYL GLYCOL DICAPRYLATE/DICAPRATE; PHENOXYETHANOL; FERRIC OXIDE RED; FERRIC OXIDE YELLOW; FERROSOFERRIC OXIDE; TITANIUM DIOXIDE

ACTIVE INGREDIENTS

Salicylic Acid 2.00%

PURPOSE

Acne Treatment

USES

Treats acne

WARNINGS

Warning
• For external use only.
• When using the product skin irritation and dryness is more likely to occur if you use another topical acne medication at the same time. If irritation occurs, only use one topical acne medication at a time.

• Keep out of reach of children. If product is swallowed, get medical help or contact a Poison Control Center right away.

Directions

• Clean the skin thoroughly before applying this product

• Cover the entire affected area with a thin layer one to three times daily

• Because excessive drying of the skin may occur, start with one application daily, then gradually increase to two or three times daily if needed or as directed by a doctor

• If bothersome dryness or peeling occurs, reduce application to once a day or every other day

• Sensitivity Test for a New User: Apply product sparingly to one or two small affected areas during first 3 days. If no discomfort occurs, follow directions above.

Inacitve Ingredients

Phenyl Trimethicone, Octyldodecanol, C12-15 Alkyl Benzoate, Stearyl Dimethicone, Euphorbia Cerifera (Candelilla) Wax, Ozokerite, Beeswax, Polyethylene, Allyl Methacrylates Crosspolymer, Tridecyl Stearate, Camellia Oleifera Leaf Extract, Ascorbyl Palmitate, Tocopherol, Tocopheryl Acetate, Retinyl Palmitate, Dimethicone, Dimethiconol, Caprylic/Capric Triglyceride, Cyclopentasiloxane, Propylene Carbonate, Disteardimonium Hectorite, Tridecyl Trimellitate, Neopentyl Glycol Dicaprylate/Dicaprate, Phenoxyethanol. (May Contain): Iron Oxides (CI 77491/77492/77499), Titanium Dioxide (CI 77891)